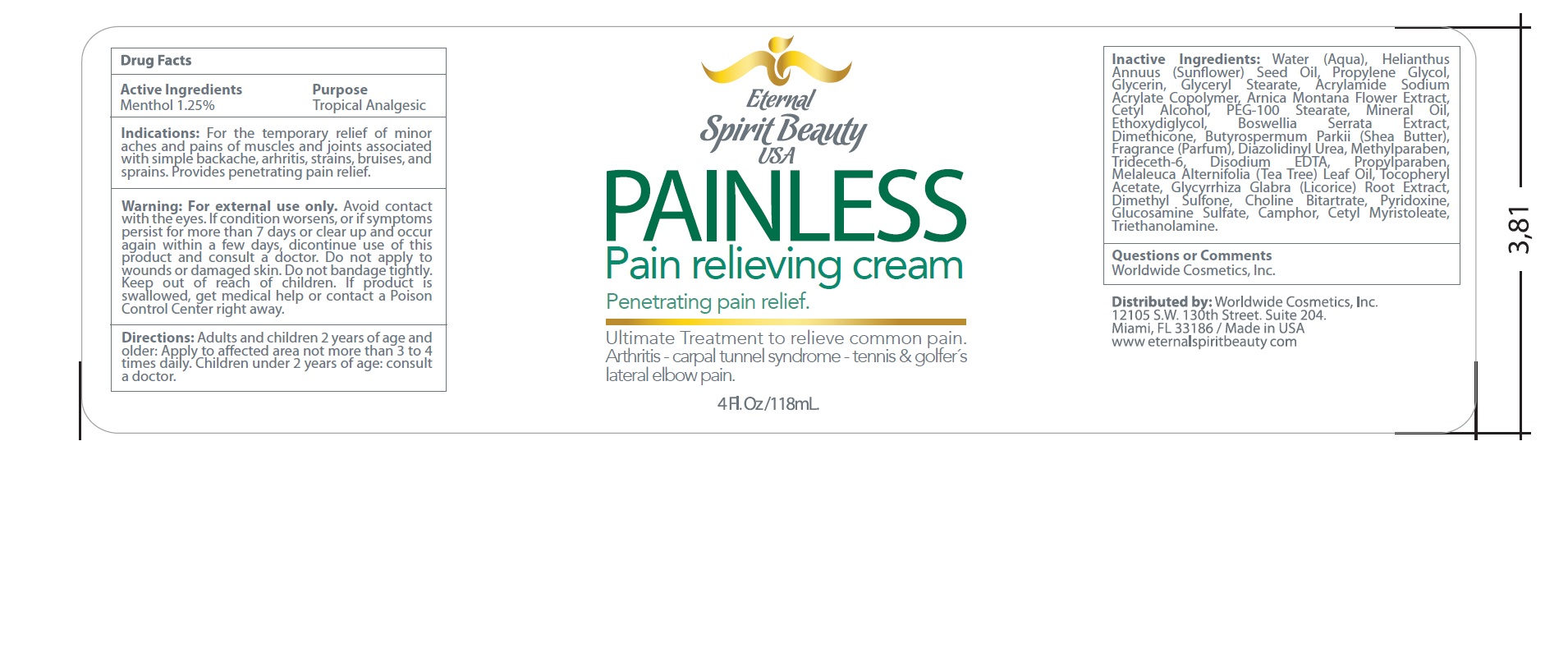 DRUG LABEL: Eternal Spirit Beauty
NDC: 58443-0223 | Form: CREAM
Manufacturer: Prime Enterprises Inc.
Category: otc | Type: HUMAN OTC DRUG LABEL
Date: 20200117

ACTIVE INGREDIENTS: MENTHOL 12.13 mg/1 mL
INACTIVE INGREDIENTS: ARNICA MONTANA FLOWER; GLYCERIN; PROPYLPARABEN; .ALPHA.-TOCOPHEROL ACETATE; GLUCOSAMINE SULFATE; DIAZOLIDINYL UREA; INDIAN FRANKINCENSE; SHEA BUTTER; METHYLPARABEN; TEA TREE OIL; CHOLINE BITARTRATE; EDETATE DISODIUM; MINERAL OIL; PYRIDOXINE; TROLAMINE; DIETHYLENE GLYCOL MONOETHYL ETHER; CETYL ALCOHOL; WATER; PEG-100 STEARATE; PROPYLENE GLYCOL; SUNFLOWER OIL; DIMETHICONE; POLYACRYLAMIDE (10000 MW); TRIDECETH-6; GLYCERYL MONOSTEARATE; LICORICE; DIMETHYL SULFONE; CAMPHOR (SYNTHETIC); CETYL MYRISTOLEATE

Eternal Spirit Beauty Painless Pain Relieving Cream

Active Ingredients

Menthol 1.25%

Purpose

Topical Analgesic

Indications:

For the temporary relief of minor aches and pains of muscles and joints associated with simple backache, arthritis, strains, bruises, and sprains. Provides penetrating pain relief.

WARNINGS

For external use only.

WHEN USING

- Avoid contact with the eyes

STOP USE

If condition worsens, or if symptoms persist for more than 7 days or clear up and occur again within a few days, discontinue use of this product and consult a doctor.

DO NOT USE

Do not apply to wounds or damaged skin. Do not bandage tightly.

Keep out of reach of children. If product is swallowed, get medical help or contact a Poison Control Center right away.

Directions

Adults and children 2 years of age and older: Apply to affected area not more than 3 to 4 times daily. Children under 2 years of age: consult a doctor.

INACTIVE INGREDIENT

Water (Aqua), Helianthus Annuus (Sunflower) Seed Oil, Propylene Glycol, Glycerin, Glyceryl Stearate, Acrylamide Sodium Acrylate Copolymer, Arnica Montana Flower Extract, Cetyl Alcohol, PEG-100 Stearate, Mineral Oil, Ethoxydiglycol, Boswellia Serrata Extract, Dimethicone, Butyrospermum Parkii (Shea Butter), Fragrance (Parfum), Diazolidinyl Urea, Methylparaben, Trideceth-6, Disodium EDTA, Propylparaben, Melaleuca Alternifolia (Tea Tree) Leaf Oil, Tocopheryl Acetate, Glycyrrhiza Glabra (Licorice) Root Extract, Dimethyl Sulfone, Choline Bitartrate, Pyridoxine, Glucosamine Sulfate, Camphor, Cetyl Myristoleate, Triethanolamine

Questions or Comments?

Worldwide Cosmetics, Inc.